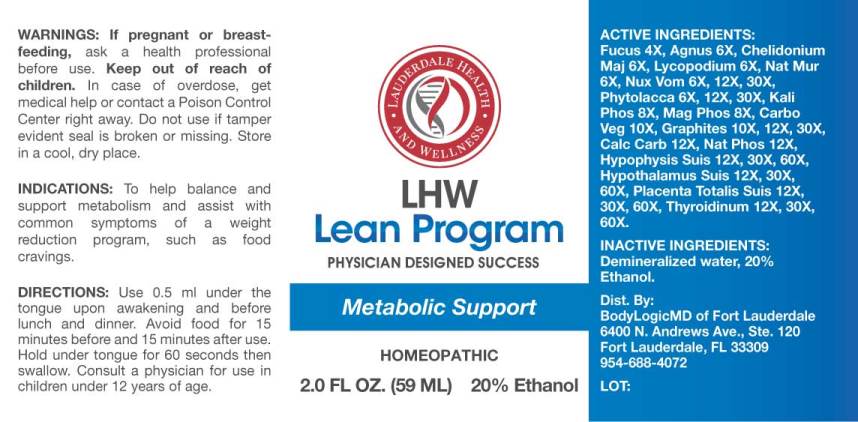 DRUG LABEL: Metabolic Support
NDC: 72250-0001 | Form: LIQUID
Manufacturer: BodyLogicMD of Fort Lauderdale
Category: homeopathic | Type: HUMAN OTC DRUG LABEL
Date: 20180608

ACTIVE INGREDIENTS: FUCUS VESICULOSUS 4 [hp_X]/1 mL; CHASTE TREE 6 [hp_X]/1 mL; CHELIDONIUM MAJUS 6 [hp_X]/1 mL; LYCOPODIUM CLAVATUM SPORE 6 [hp_X]/1 mL; SODIUM CHLORIDE 6 [hp_X]/1 mL; STRYCHNOS NUX-VOMICA SEED 6 [hp_X]/1 mL; PHYTOLACCA AMERICANA ROOT 6 [hp_X]/1 mL; DIBASIC POTASSIUM PHOSPHATE 8 [hp_X]/1 mL; MAGNESIUM PHOSPHATE, DIBASIC TRIHYDRATE 8 [hp_X]/1 mL; ACTIVATED CHARCOAL 10 [hp_X]/1 mL; GRAPHITE 10 [hp_X]/1 mL; OYSTER SHELL CALCIUM CARBONATE, CRUDE 12 [hp_X]/1 mL; SODIUM PHOSPHATE, DIBASIC, HEPTAHYDRATE 12 [hp_X]/1 mL; SUS SCROFA PITUITARY GLAND 12 [hp_X]/1 mL; SUS SCROFA HYPOTHALAMUS 12 [hp_X]/1 mL; SUS SCROFA PLACENTA 12 [hp_X]/1 mL; SUS SCROFA THYROID 12 [hp_X]/1 mL
INACTIVE INGREDIENTS: WATER; ALCOHOL

Drug Facts:

ACTIVE INGREDIENTS:

Fucus Vesiculosus 4X, Agnus Castus 6X, Chelidonium Majus 6X, Lycopodium Clavatum 6X, Natrum Muriaticum 6X, Nux Vomica 6X, 12X, 30X, Phytolacca Decandra 6X, 12X, 30X, Kali Phosphoricum 8X, Magnesia Phosphorica 8X, Carbo Vegetabilis 10X, Graphites 10X, 12X, 30X, Calcarea Carbonica 12X, Natrum Phosphoricum 12X, Hypophysis Suis 12X, 30X, 60X, Placenta Totalis Suis 12X, 30X, 60X, Thyroidinum (Suis) 12X, 30X, 60X.

INDICATIONS:

To help balance and support metabolism and assist with common symptoms of a weight reduction program, such as food cravings.

WARNINGS:

If pregnant or breast-feeding, ask a health professional before use.

Keep out of reach of children. In case of overdose, get medical help or contact a Poison Control Center right away.

Do not use if tamper evident seal is broken or missing.

Store in a cool, dry place.

Keep out of reach of children. If swallowed, get medical help or contact a Poison Control Center right away.

DIRECTIONS:

Use 0.5 ml under the tongue upon awakening and before lunch and dinner. Avoid food for 15 minutes before and 15 minutes after use. Hold under tongue for 60 seconds then swallow. Consult a physician for use in children under 12 years of age.

INDICATIONS:

To help balance and support metabolism and assist with common symptoms of a weight reduction program, such as food cravings.

INACTIVE INGREDIENTS:

Demineralized water, 20% Ethanol.

PACKAGE LABEL DISPLAY:

LHW

Lean Program

PHYSICIAN DESIGNED SUCCESS

Metabolic Support

HOMEOPATHIC

2.0 FL OZ. (59 ml)